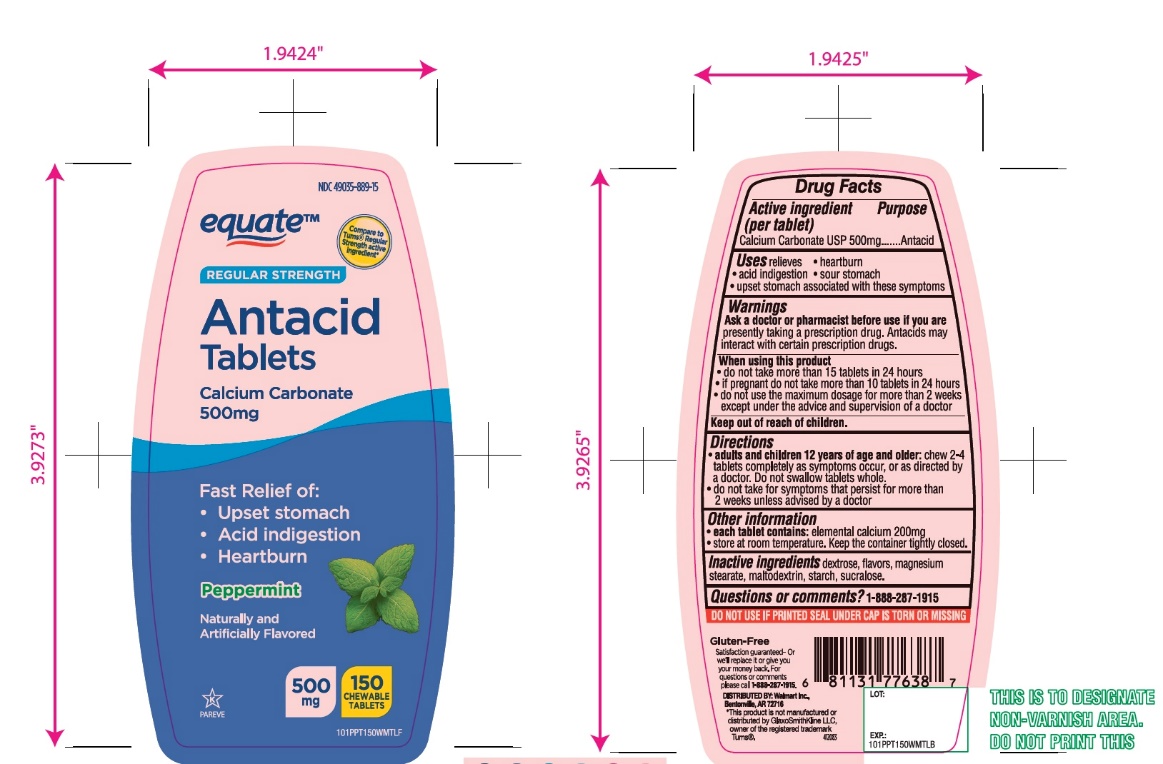 DRUG LABEL: Regular Strength Antacid
NDC: 49035-889 | Form: TABLET, CHEWABLE
Manufacturer: Wal-Mart Stores,Inc.,
Category: otc | Type: HUMAN OTC DRUG LABEL
Date: 20251027

ACTIVE INGREDIENTS: CALCIUM CARBONATE 500 mg/1 1
INACTIVE INGREDIENTS: DEXTROSE, UNSPECIFIED FORM; MAGNESIUM STEARATE; MALTODEXTRIN; STARCH, CORN; SUCRALOSE

equate™ Regular Strength Antacid Calcium Carbonate Chewable Tablets 150 Count

Active ingredient (per tablet)

Calcium Carbonate USP 500mg

Purpose

Antacid

Uses

relieves

• heartburn

• acid indigestion

• sour stomach

• upset stomach associated with these symptoms

Warnings

Ask a doctor or pharmacist before use if you arepresently taking a prescription drug. Antacids may interact with certain prescription drugs.

When using this product

- do not take more than 15 tablets in 24 hours
- if pregnant do not take more than 10 tablets in 24 hours
- do not use the maximum dosage for more than 2 weeks except under the advice and supervision of a doctor.

Directions

- adults and children 12 years of age and older:chew 2-4 tablets as symptoms occur, or as directed by a doctor. Do not swallow tablets whole.
- do not take for symptoms that persist for more than 2 weeks unless advised by a doctor

Other information

- each tablet contains:elemental calcium 200mg
- store at room temperature. Keep the container tightly closed.

Inactive ingredients

dextrose, flavors, magnesium stearate, maltodextrin, starch, sucralose .

Questions?

1-888-287-1915

SAFETY SEALED: DO NOT USE IF PRINTED SEAL UNDER CAP IS TORN OR MISSING

Package/Label Principal Display Panel

NDC 49035-889-15

Compare to Tum® Regular Strength Active Ingredient*

Regular Strength

Antacid Tablets

Calcium Carbonate 500mg

Fast Relief of:

- Upset stomach
- Acid indigestion
- Heartburn

Peppermint

Naturally and Artificially Flavored

500 mg

150 CHEWABLE TABLETS

K PAREVE

Gluten-Free

Satisfaction guaranteed- Or we’ll replace it or give you your money back.

For questions or comments, please call

1-888-287-1915.

Distributed by: Wal-Mart Inc.,

Bentonville, AR 72716

*This product is not manufactured or distributed by GlaxoSmithKline LLC, owner of the registered trademark, Tums®.